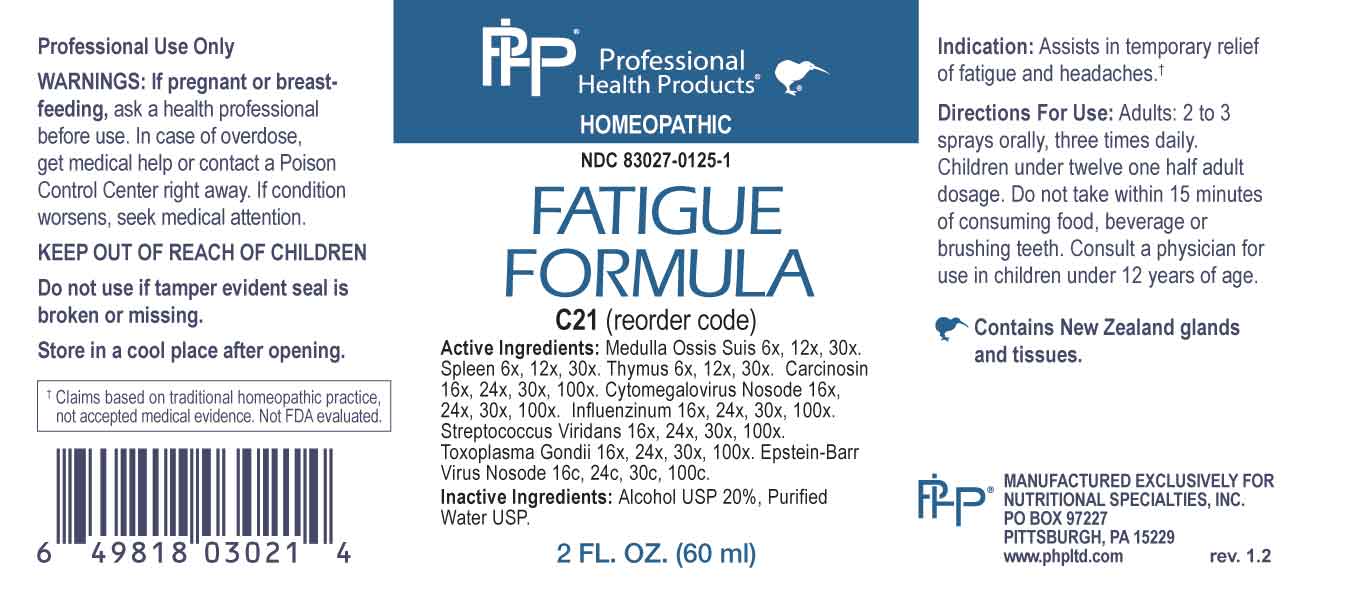 DRUG LABEL: Fatigue Formula
NDC: 83027-0125 | Form: SPRAY
Manufacturer: Nutritional Specialties, Inc.
Category: homeopathic | Type: HUMAN OTC DRUG LABEL
Date: 20241031

ACTIVE INGREDIENTS: SUS SCROFA BONE MARROW 6 [hp_X]/1 mL; BOS TAURUS SPLEEN 6 [hp_X]/1 mL; LAMB 6 [hp_X]/1 mL; HUMAN BREAST TUMOR CELL 16 [hp_X]/1 mL; HUMAN HERPESVIRUS 5 16 [hp_X]/1 mL; INFLUENZA A VIRUS A/VICTORIA/2570/2019 IVR-215 (H1N1) ANTIGEN (UV, FORMALDEHYDE INACTIVATED) 16 [hp_X]/1 mL; INFLUENZA A VIRUS A/DARWIN/9/2021 IVR-228 (H3N2) ANTIGEN (UV, FORMALDEHYDE INACTIVATED) 16 [hp_X]/1 mL; INFLUENZA B VIRUS B/AUSTRIA/1359417/2021 BVR-26 ANTIGEN (UV, FORMALDEHYDE INACTIVATED) 16 [hp_X]/1 mL; INFLUENZA B VIRUS B/PHUKET/3073/2013 ANTIGEN (UV, FORMALDEHYDE INACTIVATED) 16 [hp_X]/1 mL; STREPTOCOCCUS VIRIDANS GROUP 16 [hp_X]/1 mL; TOXOPLASMA GONDII 16 [hp_X]/1 mL; HUMAN HERPESVIRUS 4 16 [hp_C]/1 mL
INACTIVE INGREDIENTS: WATER; ALCOHOL

DRUG FACTS:

ACTIVE INGREDIENTS:

Medulla Ossis Suis 6X, 12X, 30X, Spleen 6X, 12X, 30X, Thymus 6X, 12X, 30X, Carcinosin 16X, 24X, 30X, 100X, Cytomegalovirus Nosode 16X, 24X, 30X, 100X, Influenzinum 16X, 24X, 30X, 100X, Streptococcus Viridans 16X, 24X, 30X, 100X, Toxoplasma Gondii 16X, 24X, 30X, 100X, Epstein-Bar Virus Nosode 16C, 24C, 30C, 100C.

PURPOSE:

Assists in temporary relief of fatigue and headaches.†

†Claims based on traditional homeopathic practice, not accepted medical evidence. Not FDA evaluated.

WARNINGS:

Professional Use Only

If pregnant or breast-feeding, ask a health professional before use.

In case of overdose, get medical help or contact a Poison Control Center right away.

If condition worsens, seek medical attention.

KEEP OUT OF REACH OF CHILDREN

Do not use if tamper evident seal is broken or missing.

Store in a cool place after opening

KEEP OUT OF REACH OF CHILDREN:

In case of overdose, get medical help or contact a Poison Control Center right away.

DIRECTIONS:

Adults: 2 to 3 sprays orally, three times daily. Children under twelve one half adult dosage. Do not take within 15 minutes of consuming food, beverage or brushing teeth. Consult a physician for use in children under 12 years of age.

INDICATIONS:

Assists in temporary relief of fatigue and headaches.†

†Claims based on traditional homeopathic practice, not accepted medical evidence. Not FDA evaluated.

INACTIVE INGREDIENTS:

Alcohol USP 20%, Purified Water USP.

QUESTIONS:

MANUFACTURED EXCLUSIVELY FOR

NUTRITIONAL SPECIALTIES, INC.

PO BOX 97227

PITTSBURG, PA 15229

www.phpltd.com

PACKAGE LABEL DISPLAY:

Professional

Health Products

HOMEOPATHIC

NDC 83027-0125-1

FATIGUE

FORMULA

2 FL. OZ (60 ml)